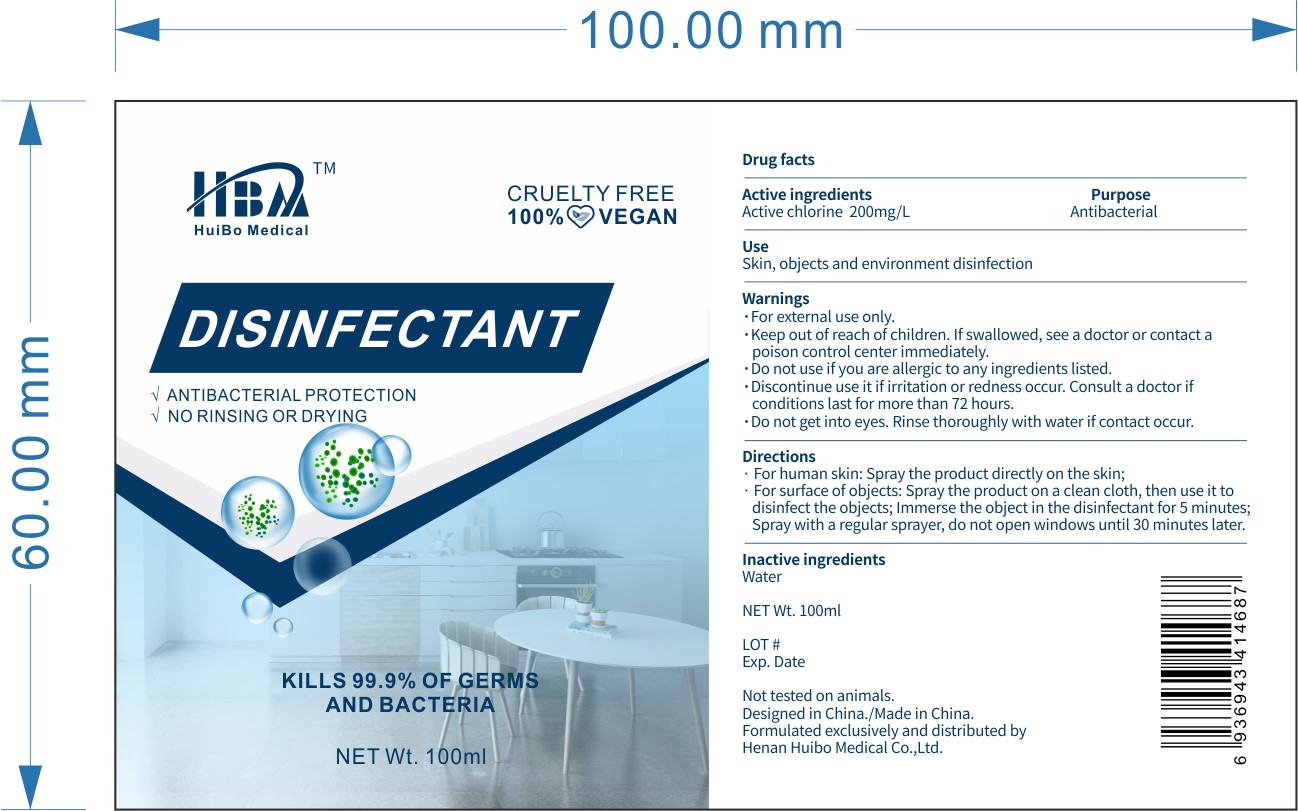 DRUG LABEL: HBA Disinfectant
NDC: 79158-002 | Form: SPRAY
Manufacturer: Henan Huibo Medical Co., Ltd.
Category: otc | Type: HUMAN OTC DRUG LABEL
Date: 20200722

ACTIVE INGREDIENTS: CHLORINE 200 mg/1000 mL
INACTIVE INGREDIENTS: WATER

Chlorine Spray

Active Ingredient

Active Chlorine 200mg/L

Purpose

Antibacterial

Use

■ Skin, object, and environment disinfection

WARNINGS

For external use only

Do not use if you are allergic to any ingredients listed

Discontinue use if irritation or redness occur. Consult a doctor if condition lasts for more than 72 hours

Do not get into eyes. Rinse thoroughly with water if contact occurs

Keep out of reach of children. If swallowed, see a doctor or contact a poison control center immediately

Directions

For human skin, spray the product directly on the skin

For surface of the objects, spray the product on a clean cloth, then use it to disinfect the objects.

Immerse the object in the disinfectant for 5 minutes.

Spray with a regular sprayer, do not open the windows until 30 minutes later

Inactive ingredients

Water